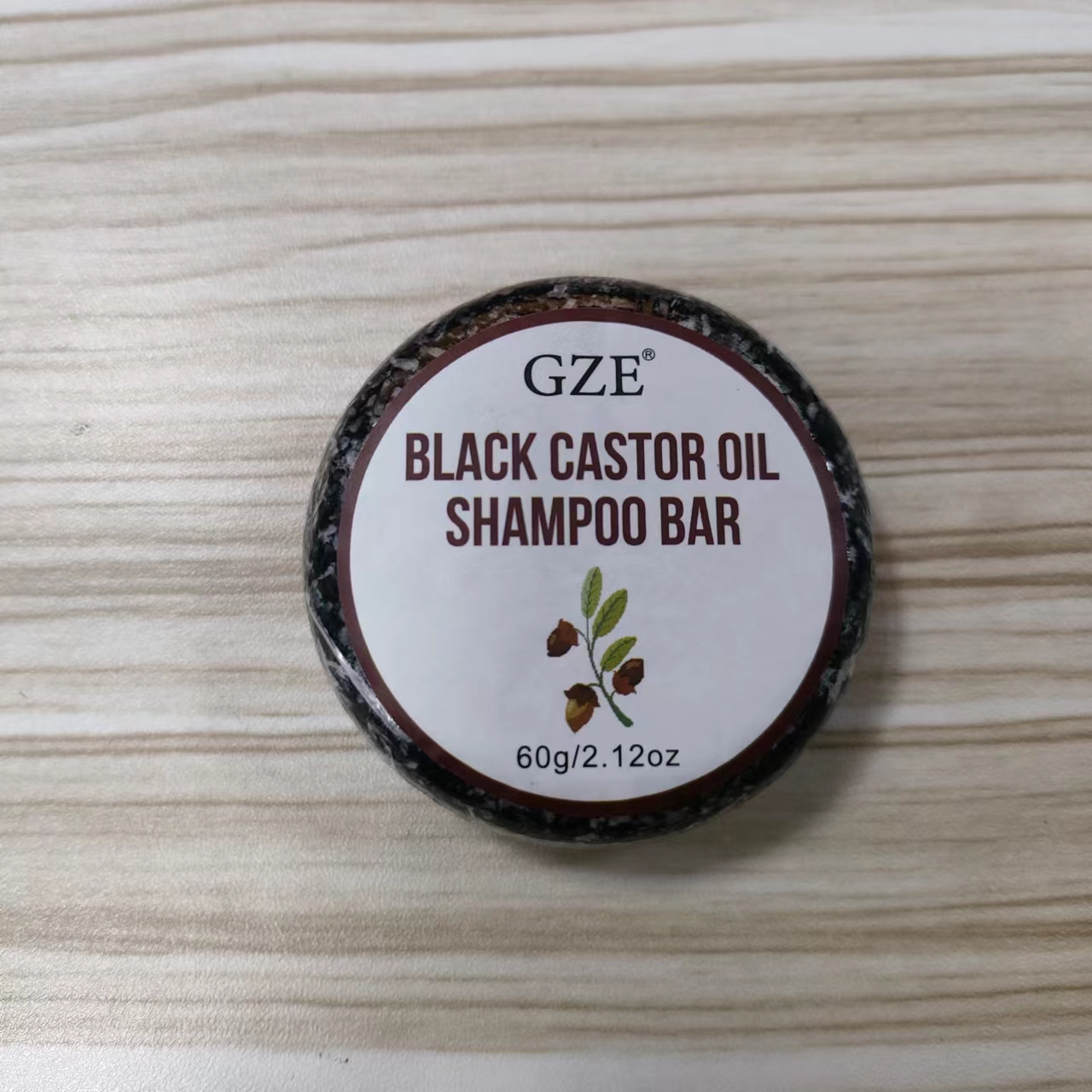 DRUG LABEL: GZE Black Castor Oil ShampooBar
NDC: 74458-170 | Form: SOAP
Manufacturer: Guangzhou Yilong Cosmetics Co., Ltd
Category: otc | Type: HUMAN OTC DRUG LABEL
Date: 20241026

ACTIVE INGREDIENTS: RICINUS COMMUNIS (CASTOR) SEED OIL 20 g/100 g
INACTIVE INGREDIENTS: THEOBROMA CACAO (COCOA) SEED BUTTER; GLYCERIN; BUTYROSPERMUM PARKII (SHEA) BUTTER; EUCALYPTUS RADIATA LEAF OIL; HYDROLYZED RICE PROTEIN (ENZYMATIC; 2000 MW)

GZE BLACK CASTOR OIL SHAMPOO BAR

ACTIVE INGREDIENT

Ricinus Communis (Castor) Seed Oil

INDICATIONS AND USAGE

To use the shampoo bar, wet your hair and rub the bar between your hands o directly onto your scalp to create a lather. Massage the lather into your scalp and hair, then rinse thoroughly with warm water.

INACTIVE INGREDIENT

Theobroma Cacao (Cocoa) Seed Butter

Glycerin

Butyrospermum Parkii (Shea) Butter

Eucalyptus Radiata Leaf/Stem Oil

Hydrolyzed Rice Protein

PURPOSE

anti-dangdruff

WARNINGS

For external use only.

Stop use and ask a doctor if rash occurs.

Do not use on damaged or broken skin.

When using this product keep out of eyes. Rinse with water to remove.

Keep out of reach of children. If swallowed, get medical help or contact a Poison Control Center right away.

DOSAGE AND ADMINISTRATION

To use the shampoo bar, wet your hair and rub the bar between your hands o directly onto your scalp to create a lather. Massage the lather into your scalp and hair, then rinse thoroughly with warm water.